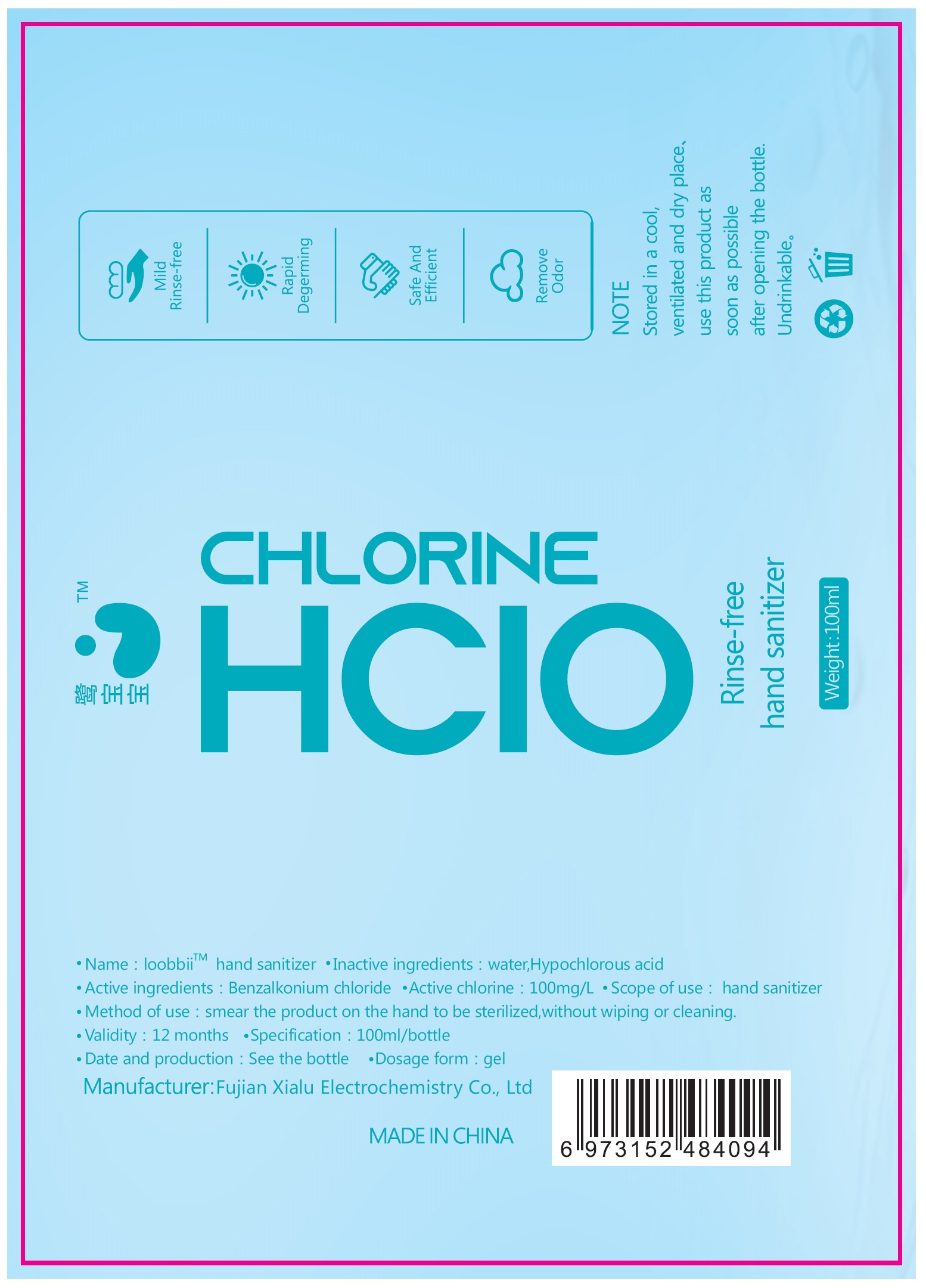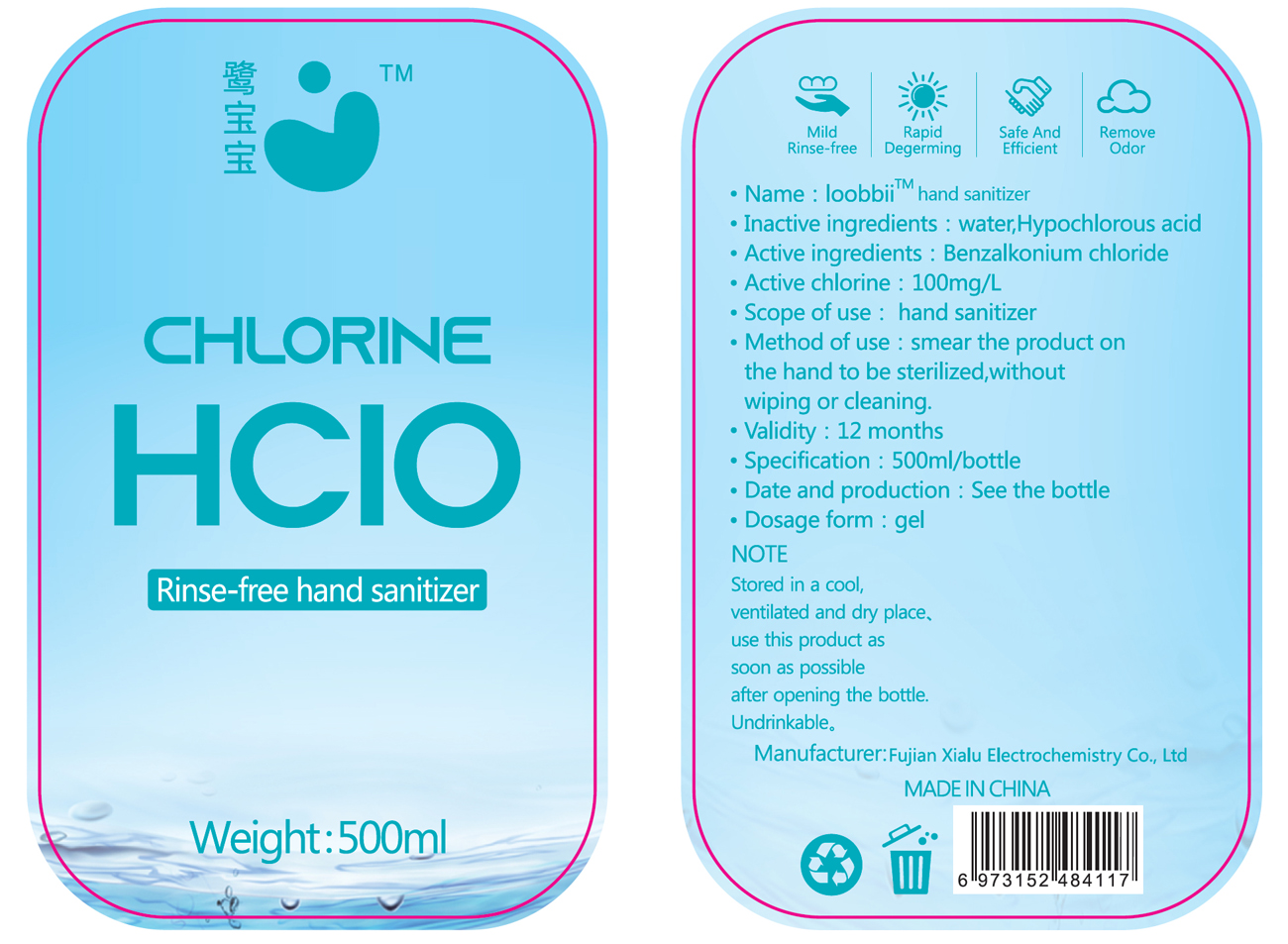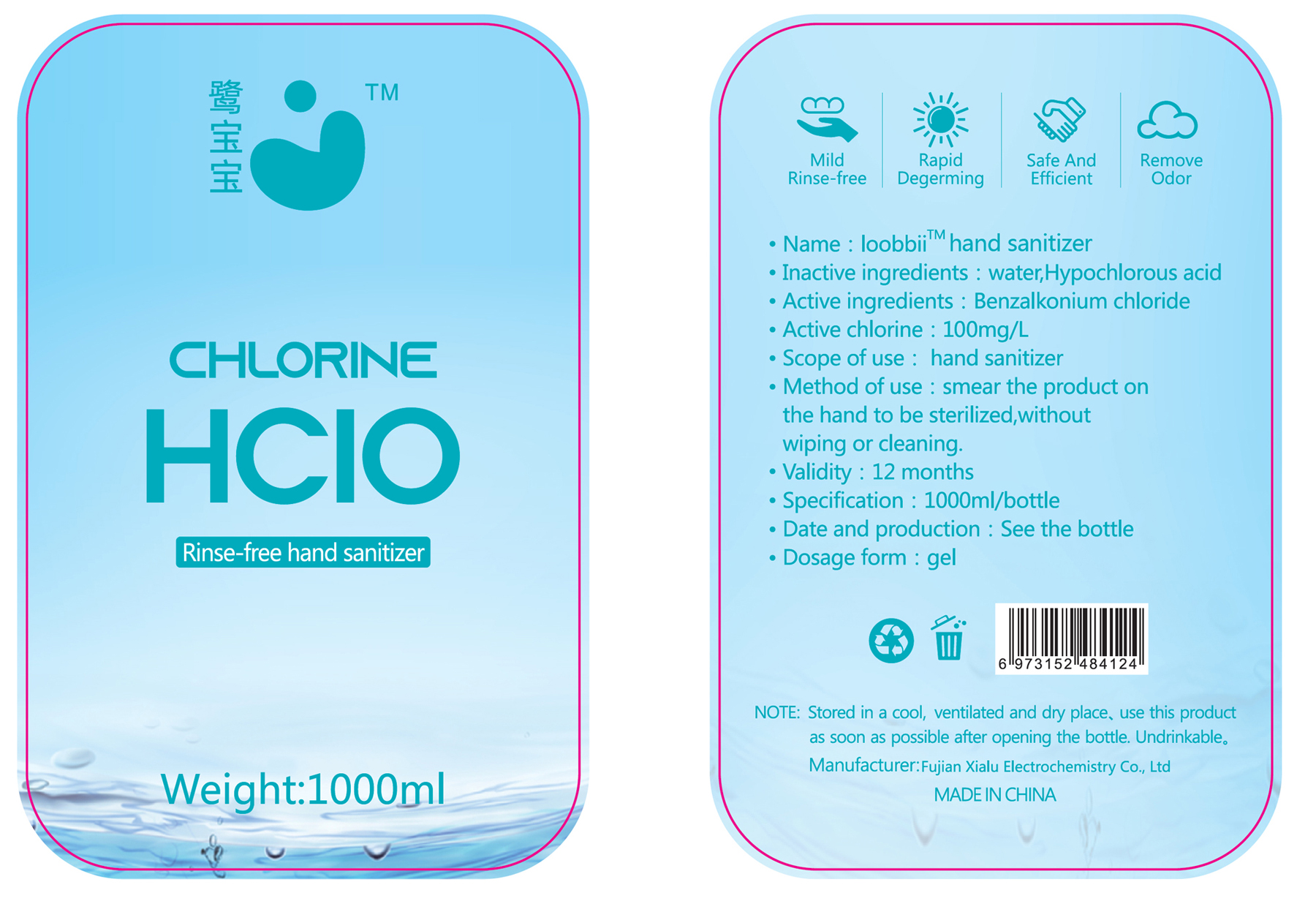 DRUG LABEL: Hand sanitizer
NDC: 75434-002 | Form: GEL
Manufacturer: Fujian Xialu Electrochemical Co., Ltd.
Category: otc | Type: HUMAN OTC DRUG LABEL
Date: 20200829

ACTIVE INGREDIENTS: BENZALKONIUM CHLORIDE 0.01 g/100 mL
INACTIVE INGREDIENTS: CARBOMER HOMOPOLYMER, UNSPECIFIED TYPE; WATER; HYPOCHLOROUS ACID

Hand sanitizer

Active Ingredients

Benzalkonium chloride

Purpose

Antiseptic

Use

Hand sanitizer

Warnings

STORED IN A COOL,VENTILATED AND DRY PLACE ,USE THIS PRODUCT AS SOON AS POSSIBLE AFTER OPENING THE BOTTLE.UNDRINKABLE.

DO NOT USE

Undrinkable

KEEP OUT OF REACH OF CHILDREN

Undrinkable

Directions

Smear the product on the hand to be sterilized, without wiping or cleaning.

Other information

STORED IN A COOL,VENTILATED AND DRY PLACE ,USE THIS PRODUCT AS SOON AS POSSIBLE AFTER OPENING THE BOTTLE.

Validity: 12 months

Date and production: See the bottle.

Dosage form: Gel

Inactive ingredients

water, hypochlorous acid

Package Label - Principal Display Panel

100ml 75434-002-01

CHLORINE

HCLO

Rinse-free

hand sanitizer

weight: 100ml

Mild Rinse-free

Rapid Degerming

Safe And Efficient

Remove Odor

500ml 75434-002-02

CHLORINE

HCLO

Rinse-free

hand sanitizer

weight: 500ml

Mild Rinse-free

Rapid Degerming

Safe And Efficient

Remove Odor

1000ml 75434-002-03

CHLORINE

HCLO

Rinse-free

hand sanitizer

weight: 1000ml

Mild Rinse-free

Rapid Degerming

Safe And Efficient

Remove Odor